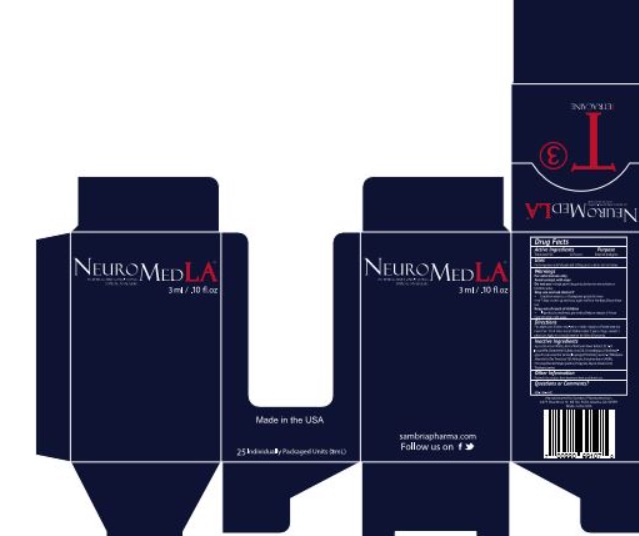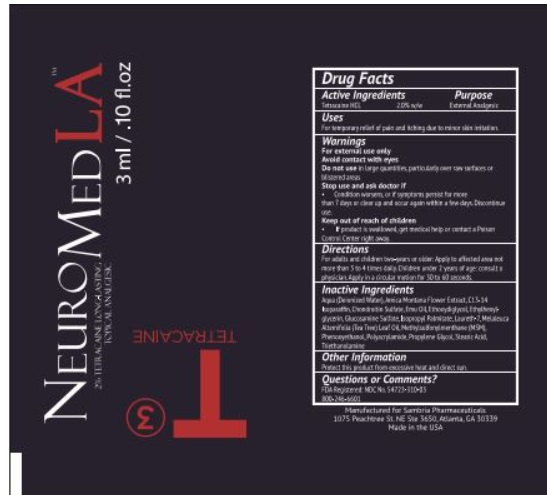 DRUG LABEL: NeuroMed Topical Analgesic



NDC: 54723-310 | Form: CREAM
Manufacturer: Sambria Pharmaceuticals, Inc.
Category: otc | Type: HUMAN OTC DRUG LABEL
Date: 20251112

ACTIVE INGREDIENTS: TETRACAINE HYDROCHLORIDE 20 mg/1000 mg
INACTIVE INGREDIENTS: WATER; ARNICA MONTANA FLOWER; C13-14 ISOPARAFFIN; CHONDROITIN SULFATE SODIUM (BOVINE); EMU OIL; DIETHYLENE GLYCOL MONOETHYL ETHER; ETHYLHEXYLGLYCERIN; GLUCOSAMINE SULFATE; ISOPROPYL PALMITATE; LAURETH-7; MELALEUCA ALTERNIFOLIA LEAF; DIMETHYL SULFONE; PHENOXYETHANOL; PROPYLENE GLYCOL; STEARIC ACID; TROLAMINE

NeuroMed LA Topical Analgesic

Active Ingredients

Tetracaine HCL 2.0% w/w

Purpose

External Analgesic

Uses

For temporary relief of pain and itching due to minor skin irritation

WARNINGS

For external use only

Avoid contact with eyes

Do not use in large quantities, particularly over raw surfaces or blistered areas

Stop use and ask a doctor if

• Condition worsens, or if symptoms persist for more then 7 days or clear up and occur again within a few days. Discontinue use.

Keep out of reach of children

• If product is swallowed, get medical help or contact a Poison Control Center right away.

Directions

For adults and children two-years or older: Apply to affected area not more than 3 to 4 times daily. Children under 2 years of age: consult a physician.

Inactive Ingredients

Aqua (Deionized Water), Arnica Montana Flower Extract, C13-14 Isoparaffin, Chondroitin Sulfate, Emu Oil, Ethoxydiglycol, Ethylhexylglycerin, Glucosamine Sulfate, Isopropyl Palmitate, Laureth-7, Melaleuca Alternifolia (Tea Tree) Leaf Oil, Methylsulfonylmethane (MSM), Phenoxyethanol, Polyacrylamide, Propylene Glycol, Stearic Acid, Triethanolamine

Other Information

Protect this product from excessive heat and direct sun.

Questions or Comments?

FDA Registered: NDC No. 54723-667-03

800-759-6876